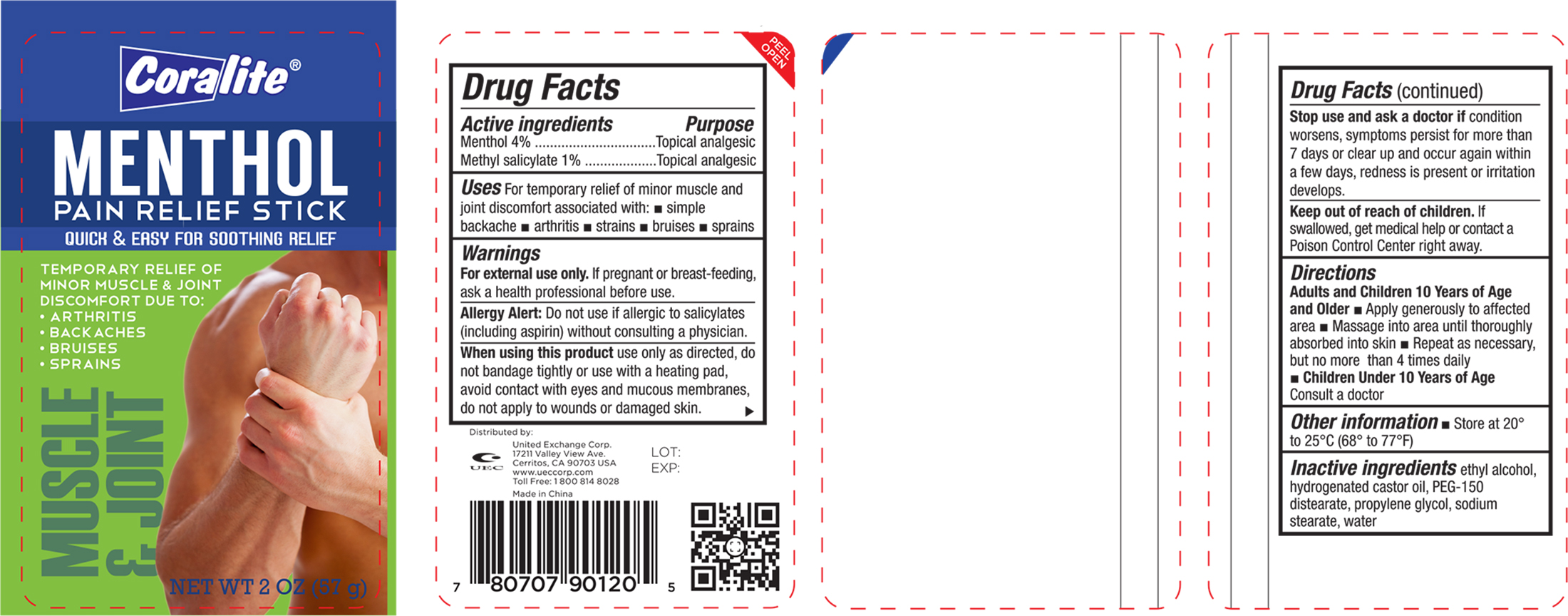 DRUG LABEL: Coralite Pain Relief Stick
NDC: 65923-120 | Form: STICK
Manufacturer: United Exchange Corp.
Category: otc | Type: HUMAN OTC DRUG LABEL
Date: 20160210

ACTIVE INGREDIENTS: MENTHOL 4 g/100 g; METHYL SALICYLATE 1 g/100 g
INACTIVE INGREDIENTS: METHYL ALCOHOL; HYDROGENATED CASTOR OIL; PEG-150 DISTEARATE; PROPYLENE GLYCOL; SODIUM STEARATE; WATER

Active ingredients Purpose

Methol 4%.......................................................Topical analgesic

Methyl salicylate 1%.........................................Topical analgesic

Uses

For temporary relief of minor muscle and joint discomfort associated with:

- simple backache
- arthritis
- strains
- bruises
- sprains

Warnings

For external use only. If pregnant or breast-feeding, ask a health professional before use.

Allergy Alert: Do not use if allergic to salicylates (including aspirin) without consulting a physician.

When using this product use only as directed, do not bandage tightly or use with a heating pad, avoid contact with eyes and mucous membranes, do not apply to wounds or damaged skin.

Stop use and ask a doctor if condition worsens, symptoms persist for more than 7 days or clear up and occur again within a few days, redness is present or irritation develops.

Keep out of reach of children. If swallowed, get medical help or contact a Poison Control Center right away.

Directions

Adults and Children 10 Years of Age and Older

- Apply generously to affected area
- Massage into area until thoroughly absorbed into skin
- Repeat as necessary, but no more than 4 times daily

Childreun Under 10 Years of Age Consult a doctor

Other information

- Store at 20° to 25°C (68° to 77°F)

INACTIVE INGREDIENT

Inactive ingredients ethyl alcohol, hydrogenated castor oil, PEG-150 distearate, propylene glycol, sodium stearate, water

DOSAGE AND ADMINISTRATION

Distributed by:

United Exchange Corp.

17211 Valley View Ave.

Cerritos, CA 90703 USA

www.ueccorp.com

Toll Free: 1 800 814 8028

Made in China